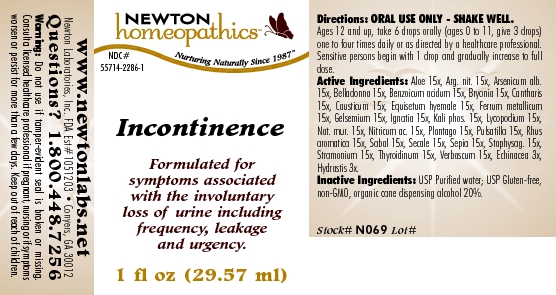 DRUG LABEL: Incontinence 
NDC: 55714-2286 | Form: LIQUID
Manufacturer: Newton Laboratories, Inc.
Category: homeopathic | Type: HUMAN OTC DRUG LABEL
Date: 20110301

ACTIVE INGREDIENTS: Aloe 15 [hp_X]/1 mL; Silver Nitrate 15 [hp_X]/1 mL; Arsenic Trioxide 15 [hp_X]/1 mL; Atropa Belladonna 15 [hp_X]/1 mL; Benzoic Acid 15 [hp_C]/1 mL; Bryonia Alba Root 15 [hp_X]/1 mL; Lytta Vesicatoria 15 [hp_X]/1 mL; Causticum 15 [hp_X]/1 mL; Equisetum Hyemale 15 [hp_X]/1 mL; Iron 15 [hp_X]/1 mL; Gelsemium Sempervirens Root 15 [hp_X]/1 mL; Strychnos Ignatii Seed 15 [hp_X]/1 mL; Potassium Phosphate, Dibasic 15 [hp_X]/1 mL; Lycopodium Clavatum Spore 15 [hp_X]/1 mL; Sodium Chloride 15 [hp_X]/1 mL; Nitric Acid 15 [hp_X]/1 mL; Plantago Major 15 [hp_X]/1 mL; Pulsatilla Vulgaris 15 [hp_X]/1 mL; Rhus Aromatica Root Bark 15 [hp_X]/1 mL; Saw Palmetto 15 [hp_X]/1 mL; Claviceps Purpurea Sclerotium 15 [hp_X]/1 mL; Sepia Officinalis Juice 15 [hp_X]/1 mL; Delphinium Staphisagria Seed 15 [hp_X]/1 mL; Datura Stramonium 15 [hp_X]/1 mL; Thyroid, Unspecified 15 [hp_X]/1 mL; Verbascum Thapsus 15 [hp_X]/1 mL; Echinacea, Unspecified 3 [hp_X]/1 mL; Goldenseal 3 [hp_X]/1 mL
INACTIVE INGREDIENTS: Alcohol

Incontinence

INDICATIONS & USAGE SECTION

Incontinence Formulated for symptoms associated with the involuntary loss of urine including frequency, leakage and urgency.

DOSAGE & ADMINISTRATION SECTION

Directions: ORAL USE ONLY - SHAKE WELL. Ages 12 and up, take 6 drops orally (ages 0 to 11, give 3 drops) one to four times daily or as directed by a healthcare professional. Sensitive persons begin with 1 drop and gradually increase to full dose.

OTC - ACTIVE INGREDIENT SECTION

Aloe 15x, Arg. nit. 15x, Arsenicum alb.15x, Belladonna 15x, Benzoicum acidum 15x, Bryonia 15x, Cantharis 15x, Causticum 15x, Equisetum hyemale 15x, Ferrum metallicum 15x, Gelsemium 15x, Ignatia 15x, Kali phos. 15x, Lycopodium 15x, Nat. mur. 15x, Nitricum ac. 15x, Plantago 15x, Pulsatilla 15x, Rhus aromatica 15x, Sabal 15x, Secale 15x, Sepia 15x, Staphysag. 15x, Stramonium 15x, Thyroidinum 15x, Verbascum 15x, Echinacea 3x, Hydrastis 3x.

OTC - PURPOSE SECTION

Formulated for symptoms associated with the involuntary loss of urine including frequency, leakage and urgency.

INACTIVE INGREDIENT SECTION

Inactive Ingredients: USP Purified Water; USP Gluten-free, non-GMO, organic cane dispensing alcohol 20%.

QUESTIONS SECTION

www.newtonlabs.net Newton Laboratories, Inc. FDA Est # 1051203 - Conyers, GA 30012
Questions? 1.800.448.7256

WARNINGS SECTION

Warning: Do not use if tamper - evident seal is broken or missing. Consult a licensed healthcare professional if pregnant, nursing or if symptoms worsen or persist for more than a few days. Keep out of reach of children

OTC - PREGNANCY OR BREAST FEEDING SECTION

Consult a licensed healthcare professional if pregnant, nursing or if symptoms worsen or persist for more than a few days.

OTC - KEEP OUT OF REACH OF CHILDREN SECTION

Keep out of reach of children.